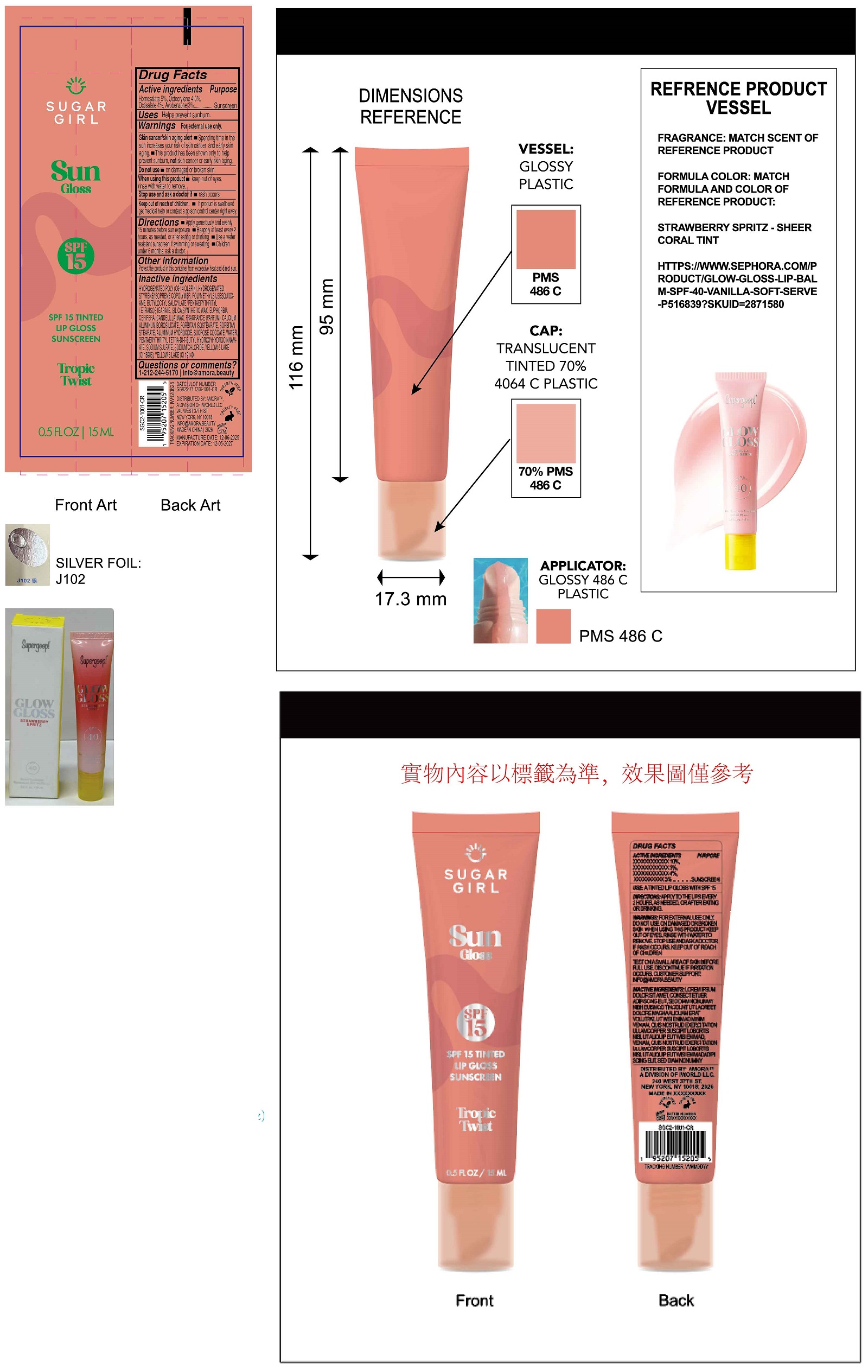 DRUG LABEL: Sugargirl Sun Gloss SPF 15 Tinted Lip Gloss Sunscreen Tropic Twist
NDC: 85179-045 | Form: LIQUID
Manufacturer: I World LLC
Category: otc | Type: HUMAN OTC DRUG LABEL
Date: 20260127

ACTIVE INGREDIENTS: HOMOSALATE 50 mg/1 mL; OCTOCRYLENE 45 mg/1 mL; OCTISALATE 40 mg/1 mL; AVOBENZONE 30 mg/1 mL
INACTIVE INGREDIENTS: BUTYLOCTYL SALICYLATE; PENTAERYTHRITYL TETRAISOSTEARATE; SILICON DIOXIDE; EUPHORBIA CERIFERA (CANDELILLA) WAX; CALCIUM ALUMINUM BOROSILICATE; SORBITAN ISOSTEARATE; SORBITAN MONOSTEARATE; ALUMINUM HYDROXIDE; SUCROSE COCOATE; WATER; PENTAERYTHRITOL TETRAKIS(3-(3,5-DI-TERT-BUTYL-4-HYDROXYPHENYL)PROPIONATE); SODIUM SULFATE; SODIUM CHLORIDE; FD&C YELLOW NO. 6 ALUMINUM LAKE; FD&C YELLOW NO. 5

Sugargirl Sun Gloss SPF 15 Tinted Lip Gloss Sunscreen Tropic Twist

Active ingredients

Homosalate 5%, Octocrylene 4.5%, Octisalate 4%, Avobenzone 3%

Purpose

Sunscreen

Uses

- Helps prevent sunburn.

Warnings

For external use only.
Skin cancer/skin aging alert

- Spending time in the sun increases your risk of skin cancer and early skin aging.
- This product has been shown only to help prevent sunburn, notskin cancer or early skin aging.

Do not use

- on damaged or broken skin.

when using this product

- keep out of eyes. rinse with water to remove.

Stop use and ask a doctor if

- rash occurs.

Keep out of reach of children.

- If product is swallowed get medical help or contact a poison control centre right away.

Directions

- Apply generously and evenly 15 minutes before sun exposer.
- Reapply at least every 2 hours.
- Use a water resistant sunscreen if swimming or sweating.
- Children under 6 month: ask a doctor.

Other information

Protect the product in this container from excessive heat and direct sun.

Inactive ingredients

HYDROGENATED POLY (C6-14 OLEFIN), HYDROGENATED STYRENE/ISOPRENE COPOLYMER, BUTYLOCTYL SALICYLATE, PENTAERYTHRITYL TETRAISOSTEARATE, SILICA, SYNTHETIC WAX, EUPHORBIA CERIFERA (CANDELILLA) WAX, FRAGRANCE (PARFUM), CALCIUM ALUMINUM BOROSILICATE, SORBITAN ISOSTEARATE, SORBITAN STEARATE, ALUMINUM HYDROXIDE, SUCROSE COCOATE, WATER, PENTAERYTHRITYL TETRA-DI-T-BUTYL HYDROXYHYDROCINNAMATE, SODIUM SULFATE, SODIUM CHLORIDE, YELLOW 6 LAKE (CI 15985), YELOW 5 LAKE (CI 19140).

Questions or comments?

1-212-244-5170 info@amora.beauty